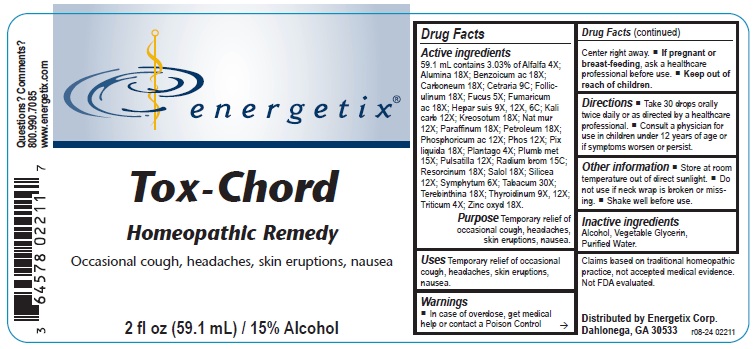 DRUG LABEL: Tox-Chord
NDC: 64578-0151 | Form: LIQUID
Manufacturer: Energetix Corporation
Category: homeopathic | Type: HUMAN OTC DRUG LABEL
Date: 20250711

ACTIVE INGREDIENTS: ALFALFA 4 [hp_X]/59.1 mL; ALUMINUM OXIDE 18 [hp_X]/59.1 mL; BENZOIC ACID 18 [hp_X]/59.1 mL; D&C BLACK NO. 2 18 [hp_X]/59.1 mL; CETRARIA ISLANDICA SUBSP. ISLANDICA 9 [hp_C]/59.1 mL; ESTRONE 18 [hp_X]/59.1 mL; FUCUS VESICULOSUS 5 [hp_X]/59.1 mL; FUMARIC ACID 18 [hp_X]/59.1 mL; PORK LIVER 9 [hp_X]/59.1 mL; POTASSIUM CARBONATE 12 [hp_X]/59.1 mL; WOOD CREOSOTE 18 [hp_X]/59.1 mL; SODIUM CHLORIDE 12 [hp_X]/59.1 mL; PARAFFIN 18 [hp_X]/59.1 mL; KEROSENE 18 [hp_X]/59.1 mL; PHOSPHORIC ACID 12 [hp_X]/59.1 mL; PHOSPHORUS 12 [hp_X]/59.1 mL; PINE TAR 18 [hp_X]/59.1 mL; PLANTAGO MAJOR 4 [hp_X]/59.1 mL; LEAD 15 [hp_X]/59.1 mL; PULSATILLA VULGARIS 12 [hp_X]/59.1 mL; RADIUM BROMIDE 15 [hp_C]/59.1 mL; RESORCINOL 18 [hp_X]/59.1 mL; PHENYL SALICYLATE 18 [hp_X]/59.1 mL; SILICON DIOXIDE 12 [hp_X]/59.1 mL; COMFREY ROOT 6 [hp_X]/59.1 mL; TOBACCO LEAF 30 [hp_X]/59.1 mL; TURPENTINE OIL 18 [hp_X]/59.1 mL; THYROID, UNSPECIFIED 9 [hp_X]/59.1 mL; ELYMUS REPENS ROOT 4 [hp_X]/59.1 mL; ZINC OXIDE 18 [hp_X]/59.1 mL
INACTIVE INGREDIENTS: ALCOHOL; GLYCERIN; WATER

Tox-Chord

ACTIVE INGREDIENT

Active ingredients 59.1 mL contains 3.03% of Alfalfa 4X; Alumina 18X; Benzoicum ac 18X; Carboneum 18X; Cetraria 9C; Folliculinum 18X; Fucus 5X; Fumaricum ac 18X; Hepar suis 9X; 12X; 6C; Kali carb 12X; Kreosotum 18X; Nat mur 12X; Paraffinum 18X; Petroleum 18X; Phosphoricum ac 12X; Phos 12X; Pix liquida 18X; Plantago 4X; Plumb met 15X; Pulsatilla 12X; Radium brom 15C; Resorcinum 18X; Salol 18X; Silicea 12X; Symphytum 6X; Tabacum 30X; Terebinthina 18X; Thyroidinum 9X; 12X; Triticum 4X; Zinc oxyd 18X.

Claims based on traditional homeopathic practice, not accepted medical evidence. Not FDA evaluated.

INDICATIONS AND USAGE

Uses Temporary relief of occasional cough, headaches, skin eruptions, nausea.

Warnings

- In case of overdose, get medical help or contact a Poison Control Center right away.
- If pregnant or breast-feeding,ask a health professional before use.

• Keep out of reach of children.

Directions

- Take 30 drops orally twice daily or as directed by a healthcare professional.
- Consult a physician for use in children under 12 years of age or if symptoms worsen or persist.

Other information

- Store at room temperature out of direct sunlight.
- Do not use if neck wrap is broken or missing.
- Shake well before use.

Inactive ingredientsAlcohol, Vegetable Glycerin, Purified Water.

QUESTIONS

Distributed by Energetix Corp.

Dahlonega, GA 30533

Questions? Comemnts?

800-990-7085

www.energetix.com

PACKAGE LABEL

Energetix

Tox-Chord

Homeopathic Remedy

Occasional cough, headaches, skin eruptions, nausea

2 fl oz (59.1 mL) / 15% Alcohol

PURPOSE

PurposeOccasional cough, headaches, skin eruptions, nausea.